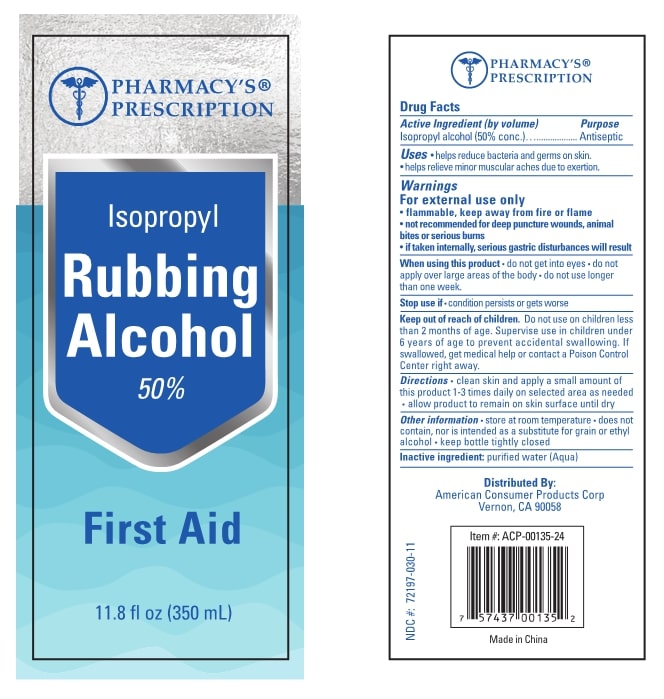 DRUG LABEL: Rubbing Alcohol
NDC: 75749-050 | Form: LIQUID
Manufacturer: Ningbo Pretty Tourism Manufacture Co., Ltd
Category: otc | Type: HUMAN OTC DRUG LABEL
Date: 20200724

ACTIVE INGREDIENTS: ISOPROPYL ALCOHOL 50 mL/100 mL
INACTIVE INGREDIENTS: WATER

Purpose

Antiseptic

Use

Hand Sanitizer to help reduce bacteria and germs on skin. helps relieve minor muscular aches due to exertion

Warnings

For external use only. Flammable. Keep away from heat or flame. Not recommended for deep puncture wounds, animal bites or serious burns. If taken internally, serious gastric disturbances will result.

Do not use

- in children less than 2 months of age
- on open skin wounds

WHEN USING

- do not get into eyes
- do not apply over large areas of the body
- do not use longer than one week

STOP USE

Condition persists or gets worse

Do not use on children less than 2 months of age. Supervise use in children under 6 years of age to prevent accidental swallowing. If swallowed, get medical help or contact a Poison Control Center right away.

Directions

- clean skin and apply a small amount of this product 1-3 daily on selected area as needed
- allow product to remain on skin surface until dry

Other information

- Store at room temperature
- does not contain, nor is intended as a substitute for grain or ethyl alcohol
- keep bottle tightly closed

Inactive ingredients

purified water (Aqua)